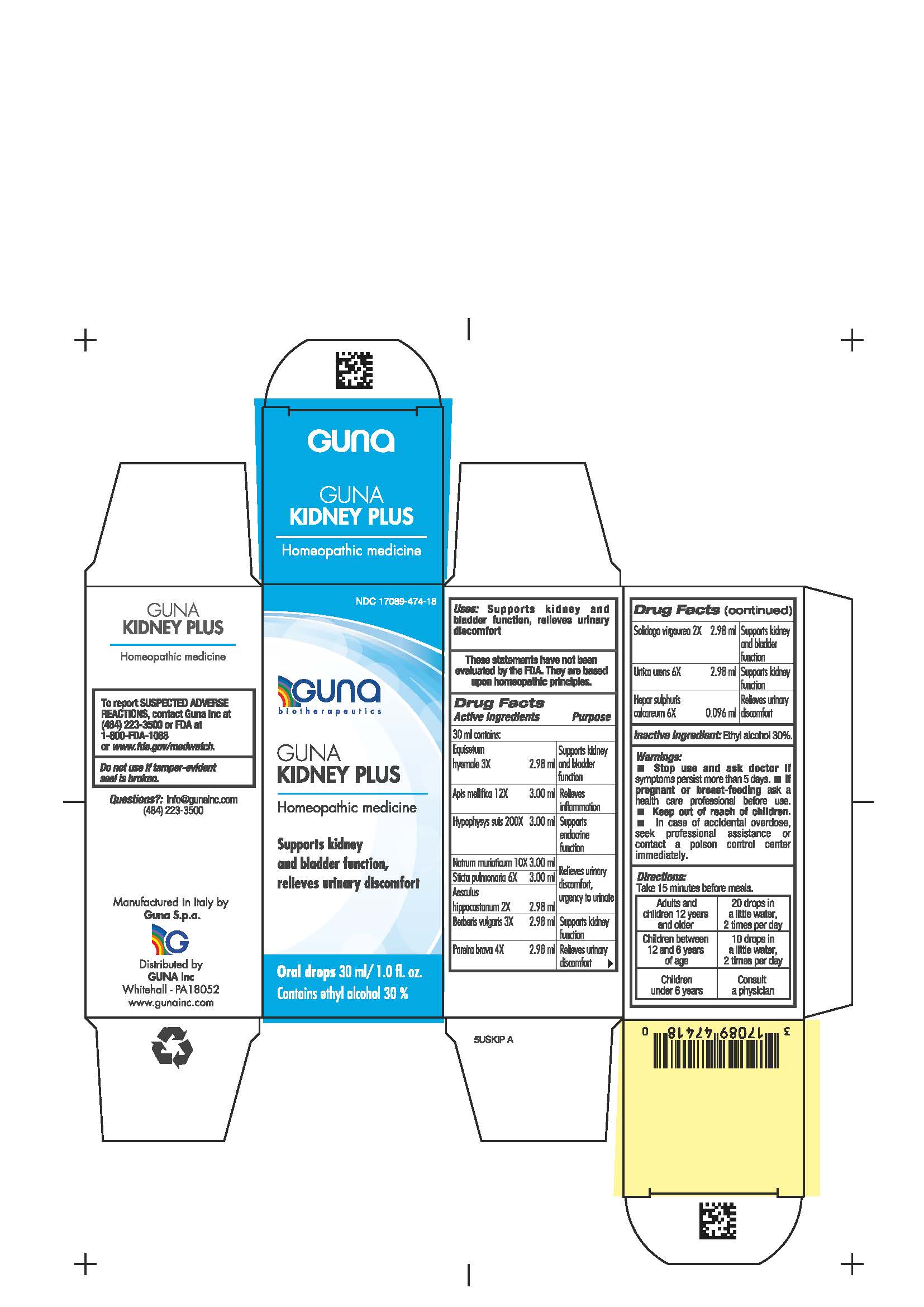 DRUG LABEL: GUNA KIDNEY PLUS
NDC: 17089-474 | Form: SOLUTION/ DROPS
Manufacturer: Guna spa
Category: homeopathic | Type: HUMAN OTC DRUG LABEL
Date: 20210204

ACTIVE INGREDIENTS: CALCIUM SULFIDE 6 [hp_X]/30 mL; EQUISETUM HYEMALE 3 [hp_X]/30 mL; SUS SCROFA PITUITARY GLAND 200 [hp_X]/30 mL; APIS MELLIFERA 12 [hp_X]/30 mL; CHONDRODENDRON TOMENTOSUM ROOT 4 [hp_X]/30 mL; SODIUM CHLORIDE 10 [hp_X]/30 mL; LOBARIA PULMONARIA 6 [hp_X]/30 mL; HORSE CHESTNUT 2 [hp_X]/30 mL; BERBERIS VULGARIS FRUIT 3 [hp_X]/30 mL; SOLIDAGO VIRGAUREA FLOWERING TOP 2 [hp_X]/30 mL; URTICA URENS 6 [hp_X]/30 mL
INACTIVE INGREDIENTS: ALCOHOL 9 mL/30 mL

GUNA KIDNEY PLUS

INDICATIONS AND USAGE

Take 15 minutes before meals

Inactive Ingredient: Ethyl alcohol 30%.

QUESTIONS

Questions?: info@gunainc.com, tel. (484) 223-3500

DIRECTIONS

Adults and children 12 years and older 20 drops in a little water, 2 times per day
Children between 12 and 6 years of age 10 drops in a little water, 2 times per day
Children under 6 years consult a physician

WARNINGS

Keep out of reach of children

PREGNANCY

If pregnant or breast-feeding ask a health care professional before use

WARNINGS

Stop use and ask doctor if symptoms persist more than 5 days.
If pregnant or breast-feeding ask a health professional before use.
Keep out of reach of children. In case of overdose, get professional assistance or contact a Poison Control Center immediately
Contains ethyl alcohol 30%

USES

- Supports kidney and bladder function,
- relieves urinary discomfort

ACTIVE INGREDIENTS/PURPOSE

Equisetum hyemale 3X Supports kidney and bladder function

Apis mellifica 12X Relieves inflammation

Hypophysys suis 200X Supports endocrine function

Natrum muriaticum 10X Relieves urinary discomfort, urgency to urinate

Sticta pulmonaria 6X Relieves urinary discomfort, urgency to urinate

Aesculus hippocastanum 2X Relieves urinary discomfort, urgency to urinate

Berberis vulgaris 3X Supports kidney function

Pareira brava 4X Relieves urinary discomfort

Solidago virgaurea 2X Supports kidney and bladder function

Urtica urens 6X Supports kidney function

Hepar sulphuris calcareum 6X Relieves urinary discomfort